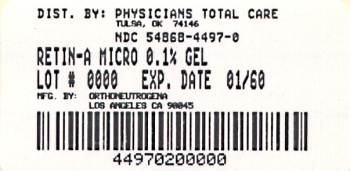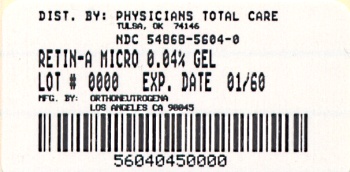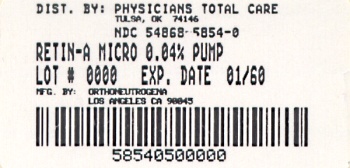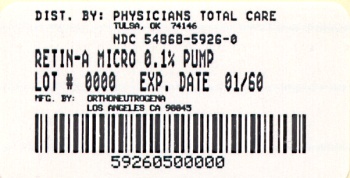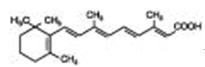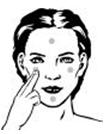 DRUG LABEL: Retin-A MICRO
NDC: 54868-4497 | Form: GEL
Manufacturer: Physicians Total Care, Inc.
Category: prescription | Type: HUMAN PRESCRIPTION DRUG LABEL
Date: 20120214

ACTIVE INGREDIENTS: Tretinoin 0.1 mg/1 g
INACTIVE INGREDIENTS: Benzyl Alcohol; Butylated Hydroxytoluene; Carbomer Homopolymer Type B; Edetate Disodium; Glycerin; Propylene Glycol; Water; Sorbic Acid; Trolamine

RETIN-A MICRO® (tretinoin gel) microsphere, 0.1% and 0.04%

FOR TOPICAL USE ONLY. NOT FOR OPHTHALMIC, ORAL, OR INTRAVAGINAL USE.

DESCRIPTION

Retin-A Micro® (tretinoin gel) microsphere, 0.1% and 0.04%, is a formulation containing 0.1% or 0.04%, by weight, tretinoin for topical treatment of acne vulgaris. This formulation uses patented methyl methacrylate/glycol dimethacrylate crosspolymer porous microspheres (MICROSPONGE® System) to enable inclusion of the active ingredient, tretinoin, in an aqueous gel. Other components of this formulation are purified water, carbomer 974P (0.04% formulation), carbomer 934P (0.1% formulation), glycerin, disodium EDTA, propylene glycol, sorbic acid, PPG-20 methyl glucose ether distearate, cyclomethicone and dimethicone copolyol, benzyl alcohol, trolamine, and butylated hydroxtoluene.

Chemically, tretinoin is all-trans-retinoic acid, also known as (all-E)-3,7-dimethyl-9-(2,6,6-trimethyl-1-cyclohexen-1-yl)-2,4,6,8-nonatetraenoic acid. It is a member of the retinoid family of compounds, and a metabolite of naturally occurring Vitamin A. Tretinoin has a molecular weight of 300.44. Tretinoin has the following structure:

CLINICAL PHARMACOLOGY

Tretinoin is a retinoid metabolite of Vitamin A that binds to intracellular receptors in the cytosol and nucleus, but cutaneous levels of tretinoin in excess of physiologic concentrations occur following application of a tretinoin-containing topical drug product.

Although tretinoin activates three members of the retinoid acid (RAR) nuclear receptors (RARα, RARβ, and RARγ) which may act to modify gene expression, subsequent protein synthesis, and epithelial cell growth and differentiation, it has not been established whether the clinical effects of tretinoin are mediated through activation of retinoic acid receptors, other mechanisms, or both.

Mode of Action

Although the exact mode of action of tretinoin is unknown, current evidence suggests that the effectiveness of tretinoin in acne is due primarily to its ability to modify abnormal follicular keratinization. Comedones form in follicles with an excess of keratinized epithelial cells. Tretinoin promotes detachment of cornified cells and the enhanced shedding of corneocytes from the follicle. By increasing the mitotic activity of follicular epithelia, tretinoin also increases the turnover rate of thin, loosely-adherent corneocytes. Through these actions, the comedo contents are extruded and the formation of the microcomedo, the precursor lesion of acne vulgaris, is reduced.

Additionally, tretinoin acts by modulating the proliferation and differentiation of epidermal cells. These effects are mediated by tretinoin's interaction with a family of nuclear retinoic receptors. Activation of these nuclear receptors causes changes in gene expression. The exact mechanisms whereby tretinoin-induced changes in gene expression regulate skin function are not understood.

Pharmacokinetics

Tretinoin is a metabolite of Vitamin A metabolism in man.

Percutaneous absorption, as determined by the cumulative excretion of radiolabeled drug into urine and feces, was assessed in 44 healthy men and women. Estimates of in vivo bioavailability, mean (SD)%, following both single and multiple daily applications, for a period of 28 days with the 0.1% gel, were 0.82 (0.11)% and 1.41 (0.54)%, respectively. The plasma concentrations of tretinoin and its metabolites, 13-cis-retinoic acid, all-trans-4-oxo-retinoic acid, and 13-cis-4-oxo-retinoic acid, generally ranged from 1 to 3 ng/mL and were essentially unaltered after either single or multiple daily applications of Retin-A Micro® (tretinoin gel) microsphere, 0.1%, relative to baseline levels. Clinical pharmacokinetic studies have not been performed with Retin-A Micro® (tretinoin gel) microsphere, 0.04%.

INDICATIONS AND USAGE

Retin-A Micro® (tretinoin gel) microsphere, 0.1% and 0.04%, is indicated for topical application in the treatment of acne vulgaris. The safety and efficacy of the use of this product in the treatment of other disorders have not been established.

CLINICAL STUDIES

Retin-A Micro® (tretinoin gel) microsphere, 0.1%

In two vehicle-controlled studies, Retin-A Micro® (tretinoin gel) microsphere, 0.1%, applied once daily was significantly more effective than vehicle in reducing the severity of acne lesion counts. The mean reductions in lesion counts from baseline after treatment for 12 weeks are shown in the following table:

Mean Percent Reduction in Lesion Counts Retin-A Micro® (tretinoin gel) microsphere, 0.1%
 | Retin-A Micro® (tretinoin gel) microsphere, 0.1% |  | Vehicle Gel
 | Study #1 72 pts | Study #2 71 pts | Study #1 72 pts | Study #2 67 pts
Non-inflammatory lesion counts | 49% | 32% | 22% | 3%
Inflammatory lesion counts | 37% | 29% | 18% | 24%
Total lesion counts | 45% | 32% | 23% | 16%

Retin-A Micro® (tretinoin gel) microsphere, 0.1% was also significantly superior to the vehicle in the investigator's global evaluation of the clinical response. In Study #1, thirty-five percent (35%) of patients using Retin-A Micro® (tretinoin gel) microsphere, 0.1%, achieved an excellent result, as compared to eleven percent (11%) of patients on the vehicle control. In Study #2, twenty-eight percent (28%) of patients using Retin-A Micro® (tretinoin gel) microsphere, 0.1%, achieved an excellent result, as compared to nine percent (9%) of the patients on the vehicle control.

Retin-A Micro® (tretinoin gel) microsphere, 0.04%

In two vehicle-controlled clinical studies, Retin-A Micro®®(tretinoin gel) microsphere, 0.04%, applied once daily, was more effective (p< 0.05) than vehicle in reducing the acne lesion counts. The mean reductions in lesion counts from baseline after treatment for 12 weeks are shown in the following table:

Mean Percent Reduction in Lesion Counts Retin-A Micro® (tretinoin gel) microsphere, 0.04%
 | Retin-A Micro® (tretinoin gel) microsphere, 0.04% |  | Vehicle Gel
 | Study #1 108 pts | Study #2 111 pts | Study #1 110 pts | Study #2 103 pts
Non-inflammatory lesion counts | 37% | 29% | -2% | 14%
Inflammatory lesion counts | 44% | 41% | 13% | 30%
Total lesion counts | 40% | 35% | 8% | 20%

Retin-A Micro® (tretinoin gel) microsphere, 0.04%, was also superior (p<0.05) to the vehicle in the investigator's global evaluation of the clinical response. In Study #1, fourteen percent (14%) of patients using Retin-A Micro® (tretinoin gel) microsphere, 0.04%, achieved an excellent result compared to five percent (5%) of patients on vehicle control. In Study #2, nineteen percent (19%) of patients using Retin-A Micro® (tretinoin gel) microsphere, 0.04%, achieved an excellent result compared to nine percent (9%) of patients on vehicle control.

No studies were conducted comparing the efficacy of Retin-A Micro® 0.04% to Retin-A Micro® 0.1%. There is no evidence that Retin-A Micro® 0.1% is more efficacious than Retin-A Micro® 0.04% or that Retin-A Micro® 0.04% is safer than Retin-A Micro® 0.1%.

CONTRAINDICATIONS

This drug is contraindicated in individuals with a history of sensitivity reactions to any of its components. It should be discontinued if hypersensitivity to any of its ingredients is noted.

PRECAUTIONS

General

- The skin of certain individuals may become excessively dry, red, swollen, or blistered. If the degree of irritation warrants, patients should be directed to temporarily reduce the amount or frequency of application of the medication, discontinue use temporarily, or discontinue use all together. Efficacy at reduced frequencies of application had not been established. If a reaction suggesting sensitivity occurs, use of the medication should be discontinued. Excessive skin dryness may also be experienced; if so, use of an appropriate emollient during the day may be helpful.
- Unprotected exposure to sunlight, including sunlamps, should be minimized during the use of Retin-A Micro® (tretinoin gel) microsphere, 0.1% and 0.04%, and patients with sunburn should be advised not to use the product until fully recovered because of heightened susceptibility to sunlight as a result of the use of tretinoin. Patients who may be required to have considerable sun exposure due to occupation and those with inherent sensitivity to the sun should exercise particular caution. Use of sunscreen products (SPF 15) and protective clothing over treated areas are recommended when exposure cannot be avoided.
- Weather extremes, such as wind or cold, also may be irritating to patients under treatment with tretinoin.
- Retin-A Micro® (tretinoin gel) microsphere, 0.1% and 0.04%, should be kept away from the eyes, the mouth, paranasal creases of the nose, and mucous membranes.
- Tretinoin has been reported to cause severe irritation on eczematous skin and should be used with utmost caution in patients with this condition.

Information for Patients

See Patient Information Leaflet.

Drug Interactions

Concomitant topical medication, medicated or abrasive soaps and cleansers, products that have a strong drying effect, products with high concentrations of alcohol, astringents, or spices should be used with caution because of possible interaction with tretinoin. Avoid contact with the peel of limes. Particular caution should be exercised with the concomitant use of topical over-the-counter acne preparations containing benzoyl peroxide, sulfur, resorcinol, or salicylic acid with Retin-A Micro® (tretinoin gel) microsphere, 0.1% and 0.04%. It also is advisable to allow the effects of such preparations to subside before use of Retin-A Micro® (tretinoin gel) microsphere, 0.1% and 0.04%, is begun.

Carcinogenesis, Mutagenesis, Impairment of Fertility

In a 91-week dermal study in which CD-1 mice were administered 0.017% and 0.035% formulations of tretinoin, cutaneous squamous cell carcinomas and papillomas in the treatment area were observed in some female mice. These concentrations are near the tretinoin concentration of these clinical formulations (0.04% and 0.1%). A dose-related incidence of liver tumors in male mice was observed at those same doses. The maximum systemic doses associated with the administered 0.017% and 0.035% formulations are 0.5 and 1.0 mg/kg/day, respectively. These doses are two and four times the maximum human systemic dose applied topically, when normalized for total body surface area. The biological significance of these findings is not clear because they occurred at doses that exceeded the dermal maximally tolerated dose (MTD) of tretinoin and because they were within the background natural occurrence rate for these tumors in this strain of mice. There was no evidence of carcinogenic potential when 0.025 mg/kg/day of tretinoin was administered topically to mice (0.1 times the maximum human systemic dose, normalized for total body surface area). For purposes of comparisons of the animal exposure to systemic human exposure, the maximum human systemic dose applied topically is defined as 1 gram of Retin-A Micro® (tretinoin gel) microsphere, 0.1%, applied daily to a 50 kg person (0.02 mg tretinoin/kg body weight).

Dermal carcinogenicity testing has not been performed with Retin-A Micro® (tretinoin gel) microsphere, 0.04% or 0.1%.

Studies in hairless albino mice suggest that concurrent exposure to tretinoin may enhance the tumorigenic potential of carcinogenic doses of UVB and UVA light from a solar simulator. This effect has been confirmed in a later study in pigmented mice, and dark pigmentation did not overcome the enhancement of photocarcinogenesis by 0.05% tretinoin. Although the significance of these studies to humans is not clear, patients should minimize exposure to sunlight or artificial ultraviolet irradiation sources.

The mutagenic potential of tretinoin was evaluated in the Ames assay and in the in vivo mouse micronucleus assay, both of which were negative.

The components of the microspheres have shown potential for genetic toxicity and teratogenesis. EGDMA, a component of the excipient acrylates copolymer, was positive for induction of structural chromosomal aberrations in the in vitro chromosomal aberration assay in mammalian cells in the absence of metabolic activation, and negative for genetic toxicity in the Ames assay, the HGPRT forward mutation assay, and the mouse micronucleus assay.

In dermal Segment I fertility studies of another tretinoin formulation in rats, slight (not statistically significant) decreases in sperm count and motility were seen at 0.5 mg/kg/day (4 times the maximum human systemic dose applied topically, and normalized for total body surface area), and slight (not statistically significant) increases in the number and percent of nonviable embryos in females treated with 0.25 mg/kg/day (2 times the maximum human systemic dose applied topically and normalized for total body surface area) and above were observed. In oral Segment I and Segment III studies in rats with tretinoin, decreased survival of neonates and growth retardation were observed at doses in excess of 2 mg/kg/day (17 times the human topical dose normalized for total body surface area.)

Dermal fertility and perinatal development studies with Retin-A Micro® (tretinoin gel) microsphere, 0.1% or 0.04%, have not been performed in any species.

Pregnancy

Teratogenic Effects

Pregnancy Category C

In a study of pregnant rats treated with topical application of Retin-A Micro® (tretinoin gel) microsphere, 0.1%, at doses of 0.5 to 1 mg/kg/day on gestation days 6-15 (4 to 8 times the maximum human systemic dose of tretinoin normalized for total body surface area after topical administration of Retin-A Micro® (tretinoin gel) microsphere, 0.1%) some alterations were seen in vertebrae and ribs of offspring. In another study, pregnant New Zealand white rabbits were treated with Retin-A Micro® (tretinoin gel) microsphere, 0.1%, at doses of 0.2, 0.5, and 1.0 mg/kg/day, administered topically for 24 hours a day while wearing Elizabethan collars to prevent ingestion of the drug. There appeared to be increased incidences of certain alterations, including domed head and hydrocephaly, typical of retinoid-induced fetal malformations in this species, at 0.5 and 1.0 mg/kg/day. Similar malformations were not observed at 0.2 mg/kg/day, 3 times the maximum human systemic dose of tretinoin after topical administration of Retin-A Micro® (tretinoin gel) microsphere, 0.1%, normalized for total body surface area. In a repeat study of the highest topical dose (1.0 mg/kg/day) in pregnant rabbits, these effects were not seen, but a few alterations that may be associated with tretinoin exposure were seen. Other pregnant rabbits exposed topically for six hours to 0.5 or 0.1 mg/kg/day tretinoin while restrained in stocks to prevent ingestion, did not show any teratogenic effects at doses up to 17 times (1.0 mg/kg/day) the maximum human systemic dose after topical administration of Retin-A Micro® (tretinoin gel) microsphere, 0.1%, adjusted for total body surface area, but fetal resorptions were increased at 0.5 mg/kg. In addition, topical tretinoin in non Retin-A Micro® (tretinoin gel) microsphere formulations was not teratogenic in rats and rabbits when given in doses of 42 and 27 times the maximum human systemic dose after topical administration of Retin-A Micro® (tretinoin gel) microsphere, 0.1%, normalized for total body surface area, respectively, (assuming a 50 kg adult applied a daily dose of 1.0 g of 0.1% gel topically). At these topical doses, however, delayed ossification of several bones occurred in rabbits. In rats, a dose-dependent increase of supernumerary ribs was observed.

Oral tretinoin has been shown to be teratogenic in rats, mice, rabbits, hamsters, and subhuman primates. Tretinoin was teratogenic in Wistar rats when given orally or topically in doses greater than 1 mg/kg/day (8 times the maximum human systemic dose normalized for total body surface area). However, variations in teratogenic doses among various strains of rats have been reported. In the cynomolgus monkey, which metabolically is more similar to humans than other species in its handling of tretinoin, fetal malformations were reported for doses of 10 mg/kg/day or greater, but none were observed at 5 mg/kg/day (83 times the maximum human systemic dose normalized for total body surface area), although increased skeletal variations were observed at all doses. Dose-related increases in embryolethality and abortion also were reported. Similar results have also been reported in pigtail macaques.

Topical tretinoin in animal teratogenicity tests has generated equivocal results. There is evidence for teratogenicity (shortened or kinked tail) of topical tretinoin in Wistar rats at doses greater than 1 mg/kg/day (8 times the maximum human systemic dose normalized for total body surface area). Anomalies (humerus: short 13%, bent 6%, os parietal incompletely ossified 14%) have also been reported when 10 mg/kg/day was topically applied. Supernumerary ribs have been a consistent finding in rats when dams were treated topically or orally with retinoids.

There are no adequate and well-controlled studies in pregnant women. Retin-A Micro® (tretinoin gel) microsphere, 0.1% and 0.04% should be used during pregnancy only if the potential benefit justifies the potential risk to the fetus.

With widespread use of any drug, a small number of birth defect reports associated temporally with the administration of the drug would be expected by chance alone. Thirty human cases of temporally associated congenital malformations have been reported during two decades of clinical use of Retin-A Micro® (tretinoin gel) microsphere, 0.1% and 0.04%. Although no definite pattern of teratogenicity and no causal association has been established from these cases, five of the reports describe the rare birth defect category holoprosencephaly (defects associated with incomplete midline development of the forebrain). The significance of these spontaneous reports in terms of risk to the fetus is not known.

Non-Teratogenic Effects

Topical tretinoin has been shown to be fetotoxic in rabbits when administered 0.5 mg/kg/day (8 times the maximum human systemic dose applied topically and normalized for total body surface area), resulting in fetal resorptions and variations in ossification. Oral tretinoin has been shown to be fetotoxic, resulting in skeletal variations and increased intrauterine death in rats when administered 2.5 mg/kg/day (21 times the maximum human systemic dose applied topically and normalized for total body surface area).

There are, however, no adequate and well-controlled studies in pregnant women.

Animal Toxicity Studies

In male mice treated topically with Retin-A Micro® (tretinoin gel) microsphere, 0.1%, at 0.5, 2.0, or 5.0 mg/kg/day tretinoin (2, 8, or 21 times the maximum human systemic dose after topical administration of Retin-A Micro® (tretinoin gel) microsphere, 0.1%, normalized for total body surface area) for 90 days, a reduction in testicular weight, but with no pathological changes were observed at the two highest doses. Similarly, in female mice there was a reduction in ovarian weights, but without any underlying pathological changes, at 5.0 mg/kg/day (21 times the maximum human dose). In this study there was a dose-related increase in the plasma concentration of tretinoin 4 hours after the first dose. A separate toxicokinetic study in mice indicates that systemic exposure is greater after topical application to unrestrained animals than to restrained animals, suggesting that the systemic toxicity observed is probably related to ingestion. Male and female dogs treated with Retin-A Micro® (tretinoin gel) microsphere, 0.1%, at 0.2, 0.5, or 1.0 mg/kg/day tretinoin (5, 12, or 25 times the maximum human systemic dose after topical administration of Retin-A Micro® (tretinoin gel) microsphere, 0.1%, normalized for total body surface area, respectively) for 90 days showed no evidence of reduced testicular or ovarian weights or pathological changes.

Nursing Mothers

It is not known whether this drug is excreted in human milk. Because many drugs are excreted in human milk, caution should be exercised when Retin-A Micro® (tretinoin gel) microsphere, 0.1% or 0.04%, is administered to a nursing woman.

Pediatric Use

Safety and effectiveness in children below the age of 12 have not been established.

Geriatric Use

Safety and effectiveness in a geriatric population have not been established. Clinical studies of Retin-A Micro® (tretinoin gel) microspere, 0.1% and 0.04% did not include sufficient numbers of subjects aged 65 and over to determine whether they responded differently from younger subjects

ADVERSE REACTIONS

Irritation Potential

Acne clinical trial results

In separate clinical trials for each concentration, acne patients treated with Retin-A Micro® (tretinoin gel) microsphere, 0.1% or 0.04%, analysis over the twelve week period showed that cutaneous irritation scores for erythema, peeling, dryness, burning/stinging, or itching peaked during the initial two weeks of therapy, decreasing thereafter.

Approximately half of the patients treated with Retin-A Micro® (tretinoin gel) microsphere, 0.04% had cutaneous irritation at Week 2. Of those patients who did experience cutaneous side effects, most had signs or symptoms that were mild in severity (severity was ranked on a 4-point ordinal scale: 0=none, 1=mild, 2=moderate, and 3=severe). Less than 10% of patients experienced moderate cutaneous irritation and there was no severe irritation at Week 2.

In studies on Retin-A Micro® (tretinoin gel) microsphere, 0.04%, throughout the treatment period the majority of patients experienced some degree of irritation (mild, moderate, or severe) with 1% (2/225) of patients having scores indicative of a severe irritation rating; and 1.3% (3/225) of patients treated with Retin-A Micro® (tretinoin gel) microsphere, 0.04%, discontinued treatment due to irritation, which included dryness in one patient and peeling and urticaria in another.

In studies on Retin-A Micro® (tretinoin gel) microsphere, 0.1%, no more than 3% of patients had cutaneous irritation scores indicative of severe irritation rating; although, 6% (14/224) of patients treated with Retin-A Micro® (tretinoin gel) microsphere, 0.1% discontinued treatment due to irritation. Of these 14 patients, four have severe irritation after 3 to 5 days of treatment, with blistering in one patient.

Results in studies of subjects without acne

In a half-face comparison trial conducted for up to 14 days in women with sensitive skin, but without acne, Retin-A Micro® (tretinoin gel) microsphere, 0.1% was statistically less irritating than tretinoin cream, 0.1%. In addition, a cumulative 21 day irritation evaluation in subjects with normal skin showed that Retin-A Micro® (tretinoin gel) microsphere, 0.1%, had a lower irritation profile than tretinoin cream, 0.1%. The clinical significance of these irritation studies for patients with acne is not established. Comparable effectiveness of Retin-A Micro® (tretinoin gel) microsphere, 0.1% and tretinoin cream, 0.1%, has not been established. The lower irritancy of Retin-A Micro® (tretinoin gel) microsphere, 0.1% in subjects without acne may be attributable to the properties of its vehicle. The contribution of decreased irritancy by the MICROSPONGE System has not been established. No irritation studies have been performed to compare Retin-A Micro® (tretinoin gel) microsphere, 0.04%, with either Retin-A Micro® (tretinoin gel) microsphere, 0.1%, or tretinoin cream, 0.1%.

The skin of certain sensitive individuals may become excessively red, edematous, blistered, or crusted. If these effects occur, the medication should either be discontinued until the integrity of the skin is restored, or the medication should be adjusted to a level the patient can tolerate. However, efficacy has not been established for lower dosing frequencies (see DOSAGE AND ADMINISTRATION Section).

True contact allergy to topical tretinoin is rarely encountered. Temporary hyper-or hypopigmentation has been reported with repeated application of tretinoin. Some individuals have been reported to have heightened susceptibility to sunlight while under treatment with tretinoin.

OVERDOSAGE

Retin A Micro® (tretinoin gel) microsphere, 0.1% and 0.04%, is intended for topical use only. If medication is applied excessively, no more rapid or better results will be obtained and marked redness, peeling, or discomfort may occur. Oral ingestion of large amounts of the drug may lead to the same side effects as those associated with excessive oral intake of Vitamin A.

DOSAGE AND ADMINISTRATION

Retin-A Micro® (tretinoin gel) microsphere, 0.1% and 0.04%, should be applied once a day, in the evening, to the skin where acne lesions appear, using enough to cover the entire affected area lightly. Application of excessive amounts of gel may result in "caking" of the gel, and will not provide incremental efficacy.

A transitory feeling of warmth or slight stinging may be noted on application. In cases where it has been necessary to temporarily discontinue therapy or to reduce the frequency of application, therapy may be resumed or the frequency of application increased as the patient becomes able to tolerate the treatment. Frequency of application should be closely monitored by careful observation of the clinical therapeutic response and skin tolerance. Efficacy has not been established for less than once daily dosing frequencies.

During the early weeks of therapy, an apparent exacerbation of inflammatory lesions may occur. If tolerated, this should not be considered a reason to discontinue therapy. Therapeutic results may be noticed after two weeks, but more than seven weeks of therapy are required before consistent beneficial effects are observed.

Patients treated with Retin-A Micro® (tretinoin gel) microsphere, 0.1% and 0.04%, may use cosmetics, but the areas to be treated should be cleansed thoroughly before the medication is applied.

HOW SUPPLIED

Retin-A Micro® (tretinoin gel) microsphere, 0.1% tube: 20g (NDC 54868-4497-0), 45g (NDC 54868-4497-1).

Retin-A Micro® (tretinoin gel) microsphere, 0.1% pump: 50g (NDC 54868-5926-0).

Retin-A Micro® (tretinoin gel) microsphere, 0.04% tube: 20g (NDC 54868-5604-1), 45g (NDC 54868-5604-0).

Retin-A Micro® (tretinoin gel) microsphere, 0.04% pump: 50g (NDC 54868-5854-0).

Storage Conditions

Store at 15° - 25° C (59° - 77°F).

Rx only.

Ortho Dermatologics
Marketed by: Ortho Dermatologics
Division of Ortho-McNeil-Janssen Pharmaceuticals, Inc.
Los Angeles, CA 90045

RETIN-A MICRO® is a registered trademark of Ortho-McNeil Pharmaceutical, Inc.
MICROSPONGE® is a registered trademark of AMCOL International Corporation

Manufactured by: Ortho Pharmaceutical
a division of Janssen Ortho LLC.
Manati, Puerto Rico 00674-0463

© OMJPI 2010

RETIN-A MICRO® (tretinoin gel) microsphere, 0.1% and 0.04%

Additional barcode labeling by:
Physicians Total Care, Inc.
Tulsa, Oklahoma 74146

PATIENT INFORMATION

RETIN-A MICRO® (ret-in-A MY-kroe)
(tretinoin gel) microsphere, 0.1% and 0.04%
For Topical Use Only

Read this information carefully before you start to use your medicine and each time you get more medicine. There may be new information about this medicine when you get your prescription renewed. This leaflet provides a summary of the information about Retin-A Micro® (tretinoin gel) microsphere, 0.1% and 0.04%. It does not include everything there is to know about your medicine. This information does not take the place of talking with your doctor; so, if you have any questions or are not sure about something, ask your doctor or pharmacist.

What is the most important information I should know about Retin-A Micro® (tretinoin gel) microsphere, 0.1% and 0.04%?

Tell your doctor if you are pregnant, think you are pregnant, trying to get pregnant, or are breastfeeding. If you become pregnant while using Retin-A Micro® (tretinoin gel) microsphere, 0.1% and 0.04%, contact your doctor right away.

Retin-A Micro® (tretinoin gel) microsphere, 0.1% and 0.04% may make your skin very dry, red, swollen or blistered. Contact your doctor if these side effects bother you.

Use other acne medicines with Retin-A Micro® (tretinoin gel) microsphere, 0.1% and 0.04% only on your doctor's advice and follow your doctor's instructions carefully. The medicines you have used in the past might cause too much redness or peeling.

Avoid sunlight or sunlamps and medicines that may make you more sensitive to sunlight. Your doctor can help you find out if you are taking medicines that may make you more sensitive to sunlight. (See " Who should not use Retin-A Micro® (tretinoin gel) microsphere, 0.1 and 0.04%?" And " What should I avoid while using Retin-A Micro® (tretinoin gel) microsphere, 0.1% and 0.04%?")

What is Retin-A Micro® (tretinoin gel) microsphere, 0.1% and 0.04%?

Retin-A Micro® (tretinoin gel) microsphere, 0.1% and 0.04% is a prescription medicine that you put on your skin to treat acne. Acne is a condition in which the skin has blackheads, whiteheads, and other pimples.

Who should not use Retin-A Micro® (tretinoin gel) microsphere, 0.1% and 0.04%?

Do not use Retin-A Micro® (tretinoin gel) microsphere, 0.1% and 0.04% if:

- you are sunburned. Do not use Retin-A Micro® (tretinoin gel) microsphere, 0.1% and 0.04% until your skin has fully recovered.
- you have eczema or other skin conditions. Retin-A Micro® (tretinoin gel) microsphere, 0.1% and 0.04% can cause severe irritation if used on eczema.
- you are allergic to any of the ingredients in Retin-A Micro® (tretinoin gel) microsphere, 0.1% and 0.04%.

The active ingredient is tretinoin. See the list of other ingredients at the end of this leaflet.

Tell your doctor before using Retin-A Micro® (tretinoin gel) microsphere, 0.1% and 0.04% if:

- you are pregnant, planning to become pregnant, or may be pregnant.
- you are breastfeeding. We do not know if Retin-A Micro® (tretinoin gel) microsphere, 0.1% and 0.04% can pass through your milk to the baby.
- you are using any other medicines to treat your acne. Do not use other medicines unless they are recommended by your doctor. Other acne medicines used with Retin-A Micro® (tretinoin gel) microsphere, 0.1% and 0.04% may make your face more likely to be dry and red and cause it to peel.
- you are taking medicines for other health conditions. Some medicines may make your skin more sensitive to sunlight. Tell your doctor about all medicines that you are taking. (See "Who should not use Retin-A Micro® (tretinoin gel) microsphere, 0.1% and 0.04%?" And " What should I avoid while using Retin-A Micro® (tretinoin gel) microsphere, 0.1% and 0.04%?")

How should I use Retin-A Micro® (tretinoin gel) microsphere, 0.1% and 0.04%?

Wash your skin with mild, non-medicated soap and dry your skin gently. Apply Retin-A Micro® (tretinoin gel) microsphere, 0.1% and 0.04% once a day in the evening, or as directed by your doctor.

Tube: Squeeze a small amount of Retin-A Micro® (tretinoin gel) microsphere, 0.1% and 0.04% (about the size of a pea) on your fingertip. Dab Retin-A Micro® (tretinoin gel) microsphere, 0.1% and 0.04% on your forehead, chin, and both cheeks. Spread Retin-A Micro® (tretinoin gel) microsphere, 0.1% and 0.04% evenly over the entire surface of your face by gently smoothing it into your skin.

Pump: Fully depress the pump twice to dispense a small amount of Retin-A Micro® (tretinoin gel) microsphere, 0.1% and 0.04% (about the size of a pea) onto your fingertip. Dab Retin-A Micro® (tretinoin gel) microsphere, 0.1% and 0.04% on your forehead, chin and both cheeks. Spread Retin-A Micro® (tretinoin gel) microsphere, 0.1% and 0.04% evenly over the entire surface of your face by gently smoothing it into your skin.

Do not put Retin-A Micro® (tretinoin gel) microsphere, 0.1% and 0.04% near your mouth, eyes, or open sores, or on the corners of your nose. Spread Retin-A Micro® (tretinoin gel) microsphere, 0.1% and 0.04% away from these areas when putting Retin-A Micro® (tretinoin gel) microsphere, 0.1% and 0.04% on your skin.

Do not use more Retin-A Micro® (tretinoin gel) microsphere, 0.1% and 0.04% than your doctor has prescribed. Do not use Retin-A Micro® (tretinoin gel) microsphere, 0.1% and 0.04% more often than your doctor has told you. Too much Retin-A Micro® (tretinoin gel) microsphere, 0.1% and 0.04% may irritate or increase the irritation of your skin, and will not give faster or better results.

You can use a facial cream or lotion each morning after washing your face. It should contain a sun protection factor (SPF) of 15 or higher. Follow your doctor's advice because you need to use a cream or lotion that will not make your acne worse. You may use cosmetics with Retin-A Micro® (tretinoin gel) microsphere, 0.1% and 0.04%. However, clean your face before using cosmetics and remove cosmetics from your skin before using Retin-A Micro® (tretinoin gel) microsphere, 0.1% and 0.04%. Talk to your doctor about recommended cosmetics.

You may not see improvement right away. Retin-A Micro® (tretinoin gel) microsphere, 0.1% and 0.04% may work better for some patients than for others. Keep using Retin-A Micro® (tretinoin gel) microsphere, 0.1% and 0.04% even after your acne improves. You may notice some results after two weeks, but more than seven weeks of using Retin-A Micro® (tretinoin gel) microsphere, 0.1% and 0.04% are needed before you see the full benefit.

Early in therapy, you may notice new pimples. At this stage, it is important to continue using Retin-A Micro® (tretinoin gel) microsphere, 0.1% and 0.04%.

Once your acne is under control you should continue regular application of Retin-A Micro® (tretinoin gel) microsphere, 0.1% and 0.04% until your doctor instructs otherwise.

What should I avoid while using Retin-A Micro® (tretinoin gel) microsphere, 0.1% and 0.04%?

Spend as little time as possible in the sun. Use a daily sunscreen with a SPF 15 rating or higher, sun protective clothing, and a wide brimmed hat to protect you from sunlight. When outside, even on hazy days, areas treated with Retin-A Micro® (tretinoin gel) microsphere, 0.1% and 0.04% should be protected. Do not use sunlamps Retin-A Micro® (tretinoin gel) microsphere, 0.1% and 0.04% may make you get sunburned more easily. If you do get sunburned, stop using RETIN-A MICRO® (tretinoin gel) microsphere, 0.1% and 0.04% until your skin is completely back to normal. Talk to your doctor about how to protect your skin if you must be in sunlight a lot.

Avoid cold weather and wind as much as possible and use clothing to protect you from the weather. Skin treated with Retin-A Micro® (tretinoin gel) microsphere, 0.1% and 0.04% may dry out or get windburned more easily.

Avoid skin products that may dry or irritate your skin. Such products are those that contain astringents, alcohol, or spices and include certain medicated soaps, shampoos and hair permanent solutions. Avoid contact with the peel of limes. Your skin may become very dry, red, swollen, blistered, or crusted with these products. If you get severe skin irritation or skin irritation that will not go away, stop using Retin-A Micro® (tretinoin gel) microsphere, 0.1% and 0.04% and call your doctor. You should talk to your doctor about the use of all skin care products while using Retin-A Micro® (tretinoin gel) microsphere, 0.1% and 0.04%.

Avoid washing your face too often and do not scrub your face hard when washing it. Use a mild, non-medicated soap and wash gently and pat dry.

Talk to your doctor about using other acne medicines while using Retin-A Micro® (tretinoin gel) microsphere, 0.1% and 0.04% as they could cause redness or peeling.

What are the possible side effects of Retin-A Micro® (tretinoin gel) microsphere, 0.1% and 0.04%?

A brief feeling of warmth or stinging may be normal when you apply Retin-A Micro® (tretinoin gel) microsphere, 0.1% and 0.04% .

The most common side effect with Retin-A Micro® (tretinoin gel) microsphere, 0.1% and 0.04% is skin irritation. This can include skin redness, burning, stinging, itching, dryness, and peeling. Some of these side effects may go away or bother you less after you have used Retin-A Micro® (tretinoin gel) microsphere, 0.1% and 0.04% for a few weeks. Tell your doctor if these side effects become a problem. Your doctor may change your dose of Retin-A Micro® (tretinoin gel) microsphere, 0.1% and 0.04%. However, the effectiveness of Retin-A Micro® (tretinoin gel) microsphere, 0.1% and 0.04% when used less than once a day has not been proven.

There may be some mild discomfort or peeling during the early weeks of treatment. Some patients also notice that their skin begins to take on a blush. These reactions happen to about half of the people using Retin-A Micro® (tretinoin gel) microsphere, 0.1% and 0.04%. If this happens to you, it is just your skin getting used to Retin-A Micro® (tretinoin gel) microsphere, 0.1% and 0.04%. This usually improves by 4 weeks after starting treatment. These reactions can usually be lessened by following instructions carefully. If the discomfort is a problem, talk to your doctor.

Call your doctor right away if your face becomes very dry, red, swollen, or blistered. Your doctor may ask you to stop using Retin-A Micro® (tretinoin gel) microsphere, 0.1% and 0.04% for a while, change the amount of Retin-A Micro® (tretinoin gel) microsphere, 0.1% and 0.04% you are using, or change the times that you use Retin-A Micro® (tretinoin gel) microsphere, 0.1% and 0.04%.

These are not all the side effects possible with Retin-A Micro® (tretinoin gel) microsphere, 0.1% and 0.04%. For more information, ask your doctor or pharmacist.

General Information about Retin-A Micro® (tretinoin gel) microsphere, 0.1% and 0.04%.

This medicine is for your use only. Do not allow anyone else to use this medicine. Medicines are sometimes prescribed for conditions not mentioned in patient information leaflets. Do not use Retin-A Micro® (tretinoin gel) microsphere, 0.1% and 0.04% for a condition for which it was not prescribed by your doctor.

What are the ingredients of Retin-A Micro® (tretinoin gel) microsphere, 0.1% and 0.04%?

The active ingredient is tretinoin. The inactive ingredients are purified water, carbomer 974P (0.04% formulation), carbomer 934P (0.1% formulation), glycerin, disodium EDTA, propylene glycol, sorbic acid, PPG-20 methyl glucose ether distearate, cyclomethicone and dimethicone copolyol, benzyl alcohol, trolamine, and butylated hydroxytoluene.

How do I store Retin-A Micro® (tretinoin gel) microsphere, 0.1% and 0.04%?

Retin-A Micro® (tretinoin gel) microsphere, 0.1% and 0.04% should be stored at room temperature, 15°-25°C (59°-77°F).

Where can I get more information about Retin-A Micro® (tretinoin gel) microsphere, 0.1% and 0.04%?

You can ask your doctor or pharmacist for the information about Retin-A Micro® (tretinoin gel) microsphere, 0.1% and 0.04% that is written for health professionals. You can also contact OrthoDermatologics by calling their toll-free number: 877-738-4624. Call between 9:00 a.m. and 3:00 p.m. Eastern Time, Monday through Friday. Or you can visit our website: www.retinamicro.com.

Ortho Dermatologics

Marketed by: Ortho Dermatologics
Division of Ortho-McNeil-Janssen Pharmaceuticals, Inc.
Los Angeles, CA 90045

RETIN-A MICRO® is a registered trademark of Ortho-McNeil Pharmaceutical, Inc.
MICROSPONGE® is a registered trademark of AMCOL International Corporation

Manufactured by: Ortho Pharmaceutical a division of Janssen Ortho LLC. Manati, Puerto Rico 00674-0463

© OMJPI 2010

735442
201560

PRINCIPAL DISPLAY PANEL

Retin-A Micro® (tretinoin gel) microsphere, 0.1% tube

Retin-A Micro® (tretinoin gel) microsphere, 0.1% pump

Retin-A Micro® (tretinoin gel) microsphere, 0.04% tube

Retin-A Micro® (tretinoin gel) microsphere, 0.04% pump